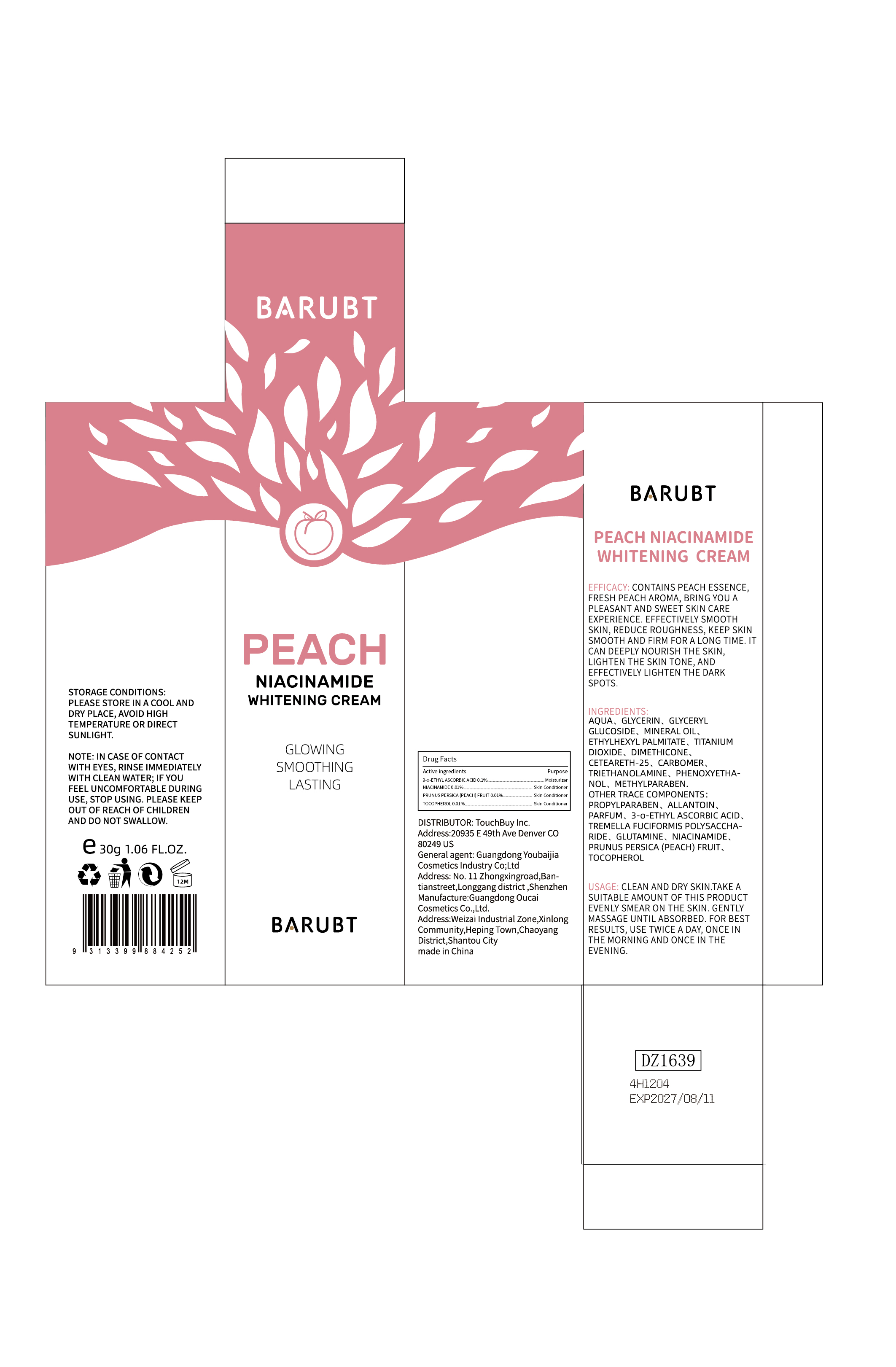 DRUG LABEL: BARUBT Peach Niacinamide Whitening Cream
NDC: 84712-031 | Form: CREAM
Manufacturer: Guangdong Youbaijia Cosmetic Industry Co., Ltd
Category: otc | Type: HUMAN OTC DRUG LABEL
Date: 20241028

ACTIVE INGREDIENTS: PRUNUS PERSICA (PEACH) FRUIT EXTRACT 0.003 g/30 g; NIACINAMIDE 0.003 g/30 g; TOCOPHEROL 0.003 g/30 g; 3-O-ETHYL ASCORBIC ACID 0.03 g/30 g
INACTIVE INGREDIENTS: GLYCERIN 1.5 g/30 g; MINERAL OIL 1.2 g/30 g

ACTIVE INGREDIENT

3-o-ETHYL ASCORBIC ACID 0.1%
NIACINAMIDE 0.01%
PRUNUS PERSICA (PEACH) FRUIT 0.01%
TOCOPHEROL 0.01%

Do not use on damaged or broken skin

INACTIVE INGREDIENT

WATER
GLYCERIN
GLYCERYL GLUCOSIDE
MINERAL OIL
ETHYLHEXYL PALMITATE
TITANIUM DIOXIDE
DIMETHICONE
CETEARETH-25
CARBOMER
TRIETHANOLAMINE
PHENOXYETHANOL
METHYLPARABEN
PROPYLPARABEN
ALLANTOIN
PARFUM
TREMELLA FUCIFORMIS POLYSACCHARIDE
GLUTAMINE

Keep away from children. Do not swallow.

PURPOSE

EFFECTIVELY SMOOTH SKIN,REDUCE ROUGHNESS,KEEP SKIN SMOOTH AND FIRM FOR A LONG TIME

QUESTIONS

Contact name: Jessie Peng
Company phone number: +1 818 579 7288
Company e-mail: jessie@registeragentllc.com

STOP USE

lf skin becomes red or irritated, discontinue use immediately and wash with water.

WHEN USING

keep out of eyes. Rinse with water to remove.

WARNINGS

For external use only.

INDICATIONS AND USAGE

EFFICACY: CONTAINS PEACH ESSENCE,FRESH PEACH AROMA, BRING YOU A PLEASANT AND SWEET SKIN CARE EXPERIENCE.EFFECTIVELY SMOOTH SKIN,REDUCE ROUGHNESS,KEEP SKINSMOOTH AND FIRM FOR A LONG TIME. IT CAN DEEPLY NOURISH THE SKIN,LIGHTEN THE SKIN TONE,AND EFFECTIVELY LIGHTEN THE DARK SPOTS.

DOSAGE AND ADMINISTRATION

USAGE: CLEAN AND DRY SKIN,TAKE A SUITABLE AMOUNT OF THIS PRODUCT EVENLY SMEAR ON THE SKIN.GENTLY MASSAGE UNTILABSORBED.FOR BEST RESULTS, USE TWICE A DAY, ONCE IN THE MORNING AND ONCE IN THE EVENING

STORAGE AND HANDLING

Storage conditions:Keep away from light and in a dry place.